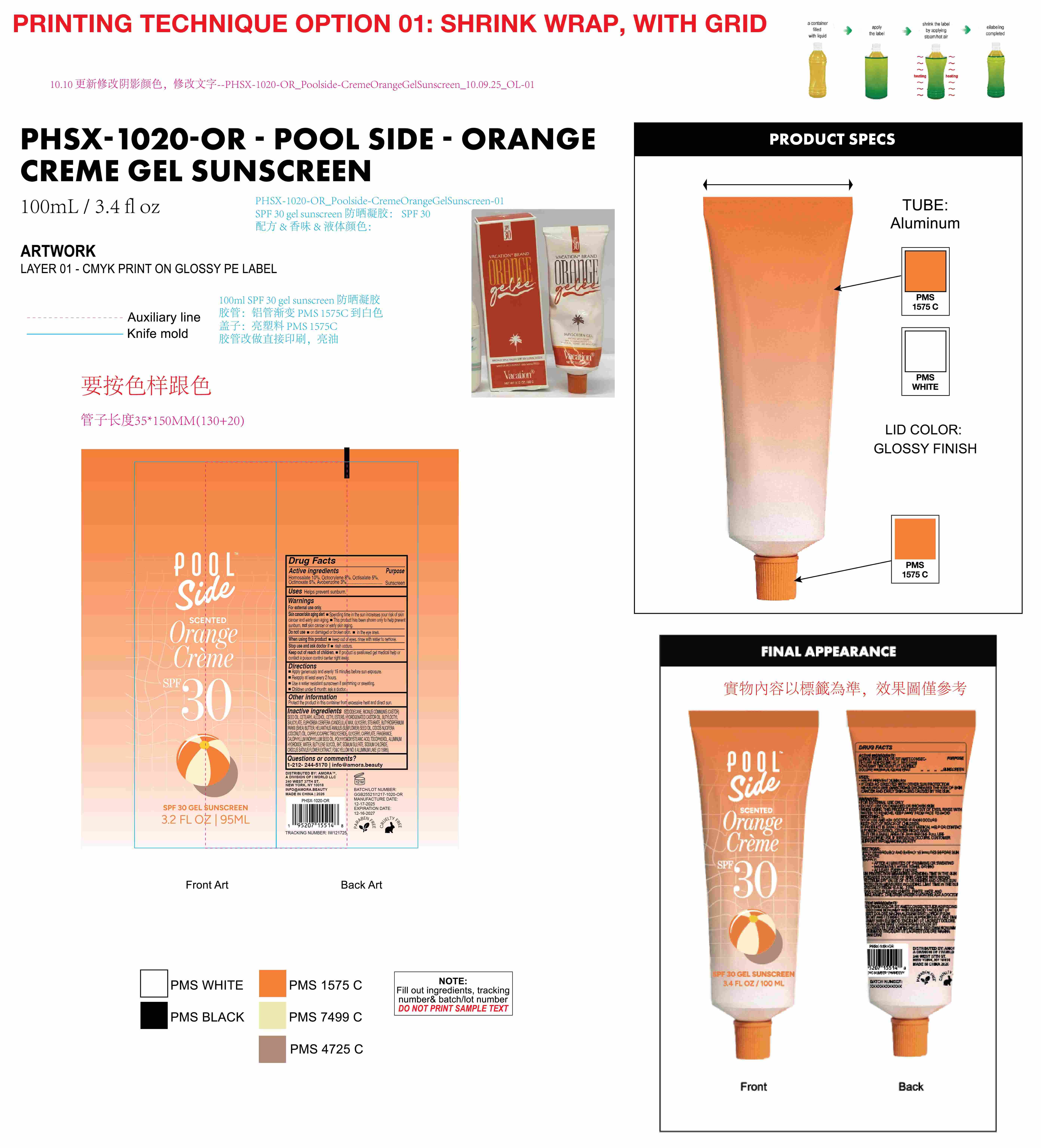 DRUG LABEL: Poolside Orange Creme SPF 30 SCENTED gel sunscreen
NDC: 85161-162 | Form: GEL
Manufacturer: Longway Technology(Guangzhou)Co.,Ltd.
Category: otc | Type: HUMAN OTC DRUG LABEL
Date: 20251204

ACTIVE INGREDIENTS: OCTISALATE 0.05 g/1 mL; AVOBENZONE 0.03 g/1 mL; HOMOSALATE 0.01 g/1 mL; OCTOCRYLENE 0.08 g/1 mL; OCTINOXATE 0.05 g/1 mL
INACTIVE INGREDIENTS: ALUMINUM HYDROXIDE; RICINUS COMMUNIS (CASTOR) SEED OIL; BUTYLENE GLYCOL; GLYCERYL STEARATE; BUTYROSPERMUM PARKII (SHEA) BUTTER; HELIANTHUS ANNUUS (SUNFLOWER) SEED OIL; GLYCERYL CAPRYLATE; TOCOPHEROL; CALOPHYLLUM INOPHYLLUM SEED OIL; CROCUS SATIVUS FLOWER; POLYHYDROXYSTEARIC ACID (2300 MW); WATER; CETEARYL ALCOHOL; CI 15985; HYDROGENATED CASTOR OIL; BUTYLOCTYL SALICYLATE; SODIUM CHLORIDE; FRAGRANCE 13576; CAPRYLIC/CAPRIC TRIGLYCERIDE; ISODODECANE; CETYL ESTERS; EUPHORBIA CERIFERA (CANDELILLA) WAX; COCOS NUCIFERA (COCONUT) OIL; BHT; SODIUM SULFATE

ACTIVE INGREDIENT

Homosalate 10%, Octocrylene 8%, Octisalate 5%,Octinoxate 5%, Avobenzone 3%

PURPOSE

Sunscreen

KEEP OUT OF REACH OF CHILDREN

If product is swallowed get medical help or contact a poison control center right away.

QUESTIONS

1-212- 244-5170 | info@amora.beauty

INDICATIONS AND USAGE

Helps prevent sunburn.

DOSAGE AND ADMINISTRATION

Apply generously and evenly 15 minutes before sun exposure.
Reapply at least every 2 hours.
Use a water resistant sunscreen if swimming or sweating.
Children under 6 month: ask a doctor.

WARNINGS

For external use only.
Spending time in the sun increases your risk of skin Skin cancer/skin aging alert cancer and early skin aging. This product has been shown only to help prevent sunburn, not skin cancer or early skin aging.

Do not use on damaged or broken skin.in the eye area.

When using this product keep out of eyes. rinse with water to remove.

Stop use and ask doctor if rash occurs.

Keep out of reach of children. If product is swallowed get medical help or contact a poison control center right away.

OTHER SAFETY INFORMATION

Protect the product in this container from excessive heat and direct sun